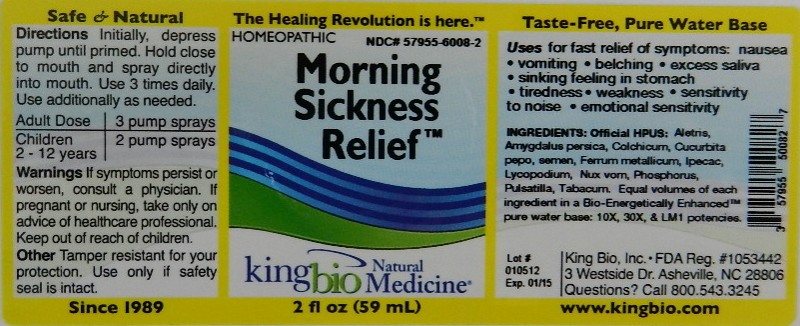 DRUG LABEL: Morning Sickness Relief
NDC: 57955-6008 | Form: LIQUID
Manufacturer: King Bio Inc.
Category: homeopathic | Type: HUMAN OTC DRUG LABEL
Date: 20120112

ACTIVE INGREDIENTS: ALETRIS FARINOSA ROOT 10 [hp_X]/59 mL; PRUNUS PERSICA FLOWER 10 [hp_X]/59 mL; COLCHICUM AUTUMNALE BULB 10 [hp_X]/59 mL; PUMPKIN SEED 10 [hp_X]/59 mL; IRON 10 [hp_X]/59 mL; IPECAC 10 [hp_X]/59 mL; LYCOPODIUM CLAVATUM SPORE 10 [hp_X]/59 mL; STRYCHNOS NUX-VOMICA SEED 10 [hp_X]/59 mL; PHOSPHORUS 10 [hp_X]/59 mL; PULSATILLA VULGARIS 10 [hp_X]/59 mL; TOBACCO LEAF 10 [hp_X]/59 mL
INACTIVE INGREDIENTS: WATER

Morning Sickness Relief

Active Ingredients

Official HPUS: Aletris farinosa, Amygdalus persica, Colchicum autumnale, Cucurbita pepo, semen, Ferrum metallicum, Ipecacuanha, Lycopodium clavatum, Nux vomica, Phosphorus, Pulsatilla and Tabacum.

Reference image morning sickness relief.jpg

Inactive Ingredient

Equal volumes of each ingredient in a Bio-Energetically Enhanced pure water base: 10X, 30X and LM1 potencies.

Reference image morning sickness relief.jpg

Purpose

Uses for fast relief of symptoms:

- nausea
- vomiting
- belching
- excess saliva
- sinking feeling in stomach
- tiredness
- weakness
- sensitivity to noise
- emotional sensitivity

Reference image morning sickness relief.jpg

Dosage and Administration

Directions: Initially, depress pump until primed. Hold close to mouth and spray directly into mouth. Use 3 times daily. Use additionally as needed.

Adult Dose 3 pump sprays

Children (2 - 12 years) 2 pump sprays

Reference image morning sickness relief.jpg

Warnings

If symptoms persist or worsen, consult a physician. If pregnant or nursing, take only on advice of healthcare professional.

Other: Tamper resistant for your protection. Use only if safety seal is intact.

Reference image morning sickness relief.jpg

Keep out of reach of children.

Reference image morning sickness relief.jpg

Indications and Usage

Uses for fast relief of symptoms: Nausea, vomiting, belching, excess saliva, sinking feeling in stomach, tiredness, weakness, sensitivity to noise and emotional sensitivity.

Reference image morning sickness relief.jpg

PACKAGE LABEL

King Bio Inc.

3 Westside Drive

Asheville, NC 28806

Questions? Call 800.543.3245

www.kingbio.com

Safe and Natural Homeopathic